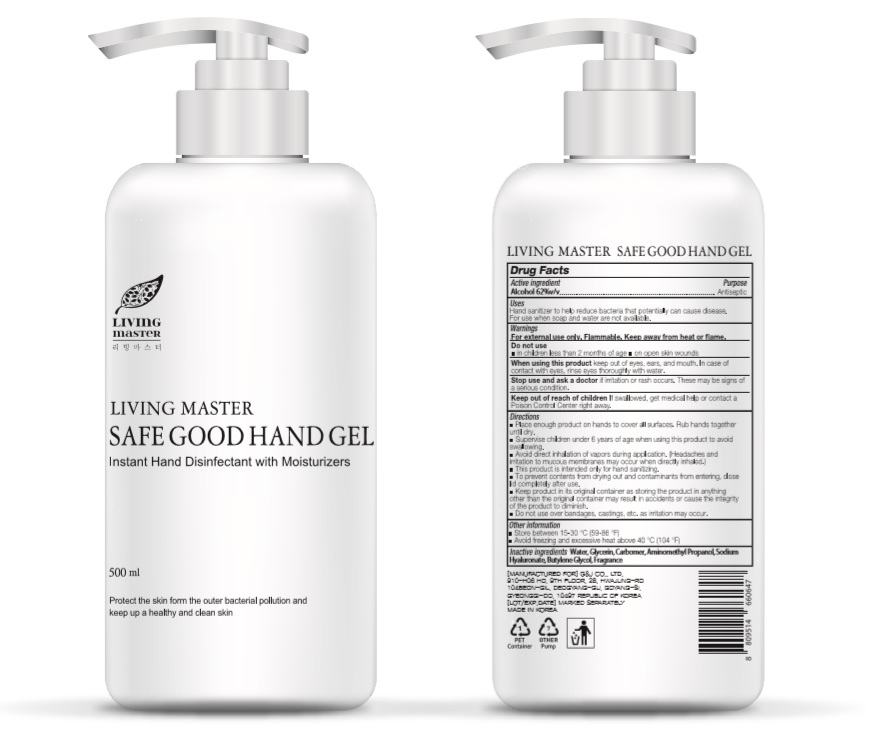 DRUG LABEL: LIVING MASTER SAFE GOOD HAND Gel
NDC: 74339-2500 | Form: GEL
Manufacturer: PL COSMETIC
Category: otc | Type: HUMAN OTC DRUG LABEL
Date: 20200423

ACTIVE INGREDIENTS: ALCOHOL 310 mL/500 mL
INACTIVE INGREDIENTS: GLYCERIN; CARBOMER HOMOPOLYMER, UNSPECIFIED TYPE; WATER; BUTYLENE GLYCOL; HYALURONATE SODIUM; AMINOMETHYLPROPANOL

LIVING MASTER SAFE GOOD HAND GEL 500 ml : 74339-2500-1